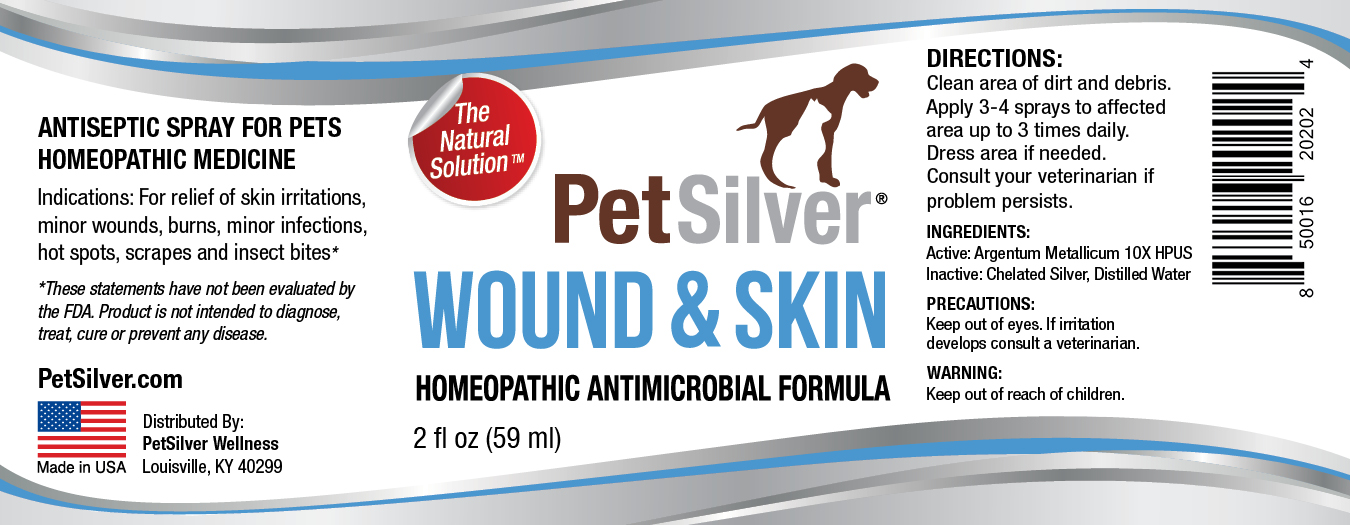 DRUG LABEL: PetSilver Wound 2
NDC: 72363-016 | Form: SPRAY
Manufacturer: AG Essence
Category: homeopathic | Type: HUMAN OTC DRUG LABEL
Date: 20251214

ACTIVE INGREDIENTS: SILVER 0.00175 g/59 g
INACTIVE INGREDIENTS: ANHYDROUS CITRIC ACID 0.009 g/59 g; WATER 58.98925 g/59 g

PetSilver Wound Spray 2 ounces

DIRECTIONS:

Clean area of dirt and debris. Apply 3-4 sprays to affected area up to 3 times daily. Dress area if needed. Consult your veterinarian if problem persists.

PRECAUTIONS

Keep out of eyes. If irritation develops consult a veterinarian.

INGREDIENT:

Active: Argentum Metallicum10X HPUS

INGREDIENTS:

Inactive: Chelated silver, Distilled Water

Indications:

For relief of skin irritations, minor wounds, burns, minor infections, hot spots, scrapes and insect bites.

WARNING:

Keep out of reach of children

WARNING:

Keep out of reach of children